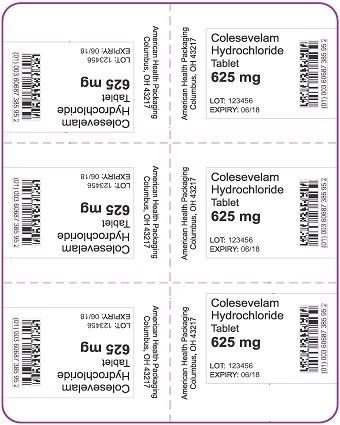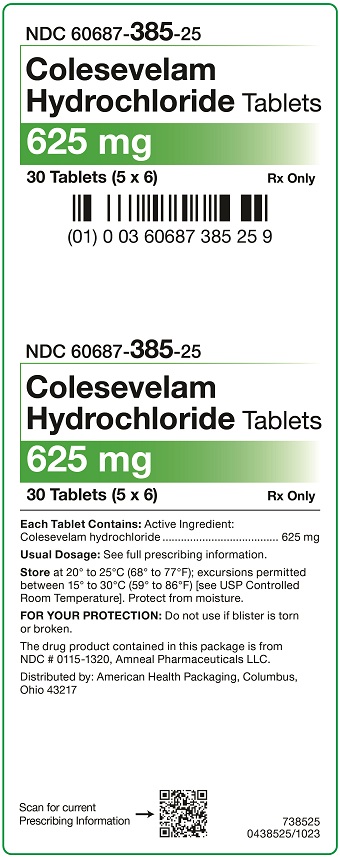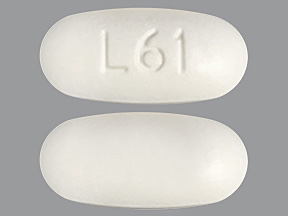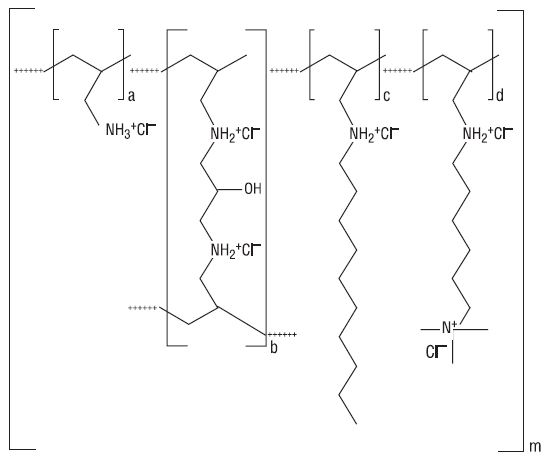 DRUG LABEL: Colesevelam Hydrochloride
NDC: 60687-385 | Form: TABLET, FILM COATED
Manufacturer: American Health Packaging
Category: prescription | Type: HUMAN PRESCRIPTION DRUG LABEL
Date: 20251205

ACTIVE INGREDIENTS: COLESEVELAM HYDROCHLORIDE 625 mg/1 1
INACTIVE INGREDIENTS: SILICON DIOXIDE; COPOVIDONE K25-31; HYPROMELLOSE 2910 (6 MPA.S); HYPROMELLOSE 2910 (15 MPA.S); MAGNESIUM STEARATE; MICROCRYSTALLINE CELLULOSE; POLYETHYLENE GLYCOL 6000; TALC

HIGHLIGHTS OF PRESCRIBING INFORMATION

These highlights do not include all the information needed to use COLESEVELAM HYDROCHLORIDE TABLETS safely and effectively. See full prescribing information for COLESEVELAM HYDROCHLORIDE TABLETS.
COLESEVELAM HYDROCHLORIDE tablets, for oral use
Initial U.S. Approval: 2000

1 INDICATIONS AND USAGE

Colesevelam hydrochloride is a bile acid sequestrant indicated as an adjunct to diet and exercise to:

- reduce elevated low-density lipoprotein cholesterol (LDL-C) in adults with primary hyperlipidemia. (1.1)
- reduce LDL-C levels in boys and postmenarchal girls, 10 to 17 years of age, with heterozygous familial hypercholesterolemia (HeFH), unable to reach LDL-C target levels despite an adequate trial of diet and lifestyle modification. (1.1)

Limitations of Use (1.3):

- Do not use for treatment of type 1 diabetes or for diabetic ketoacidosis.
- Not studied in Fredrickson Type I, III, IV, and V dyslipidemias.

2 DOSAGE AND ADMINISTRATION

- Obtain lipid parameters, including serum triglyceride (TG) levels, before starting colesevelam hydrochloride tablets. (2.1)
- The recommended dosage for adults and for boys and postmenarchal girls aged 10 to 17 years with primary hyperlipidemia is 3.75 grams daily. Colesevelam hydrochloride tablets should be taken as follows (2.2, 2.4):

Tablets
Take 6 tablets once daily or 3 tablets twice daily with a meal and liquid.

3 DOSAGE FORMS AND STRENGTHS

- Tablets: 625 mg. (3)

4 CONTRAINDICATIONS

- Patients with serum triglyceride levels > 500 mg/dL. (4)
- Patients with a history of hypertriglyceridemia-induced pancreatitis. (4)
- Patients with a history of bowel obstruction. (4)

5 WARNINGS AND PRECAUTIONS

- Hypertriglyceridemia and Pancreatitis: Colesevelam hydrochloride can increase TG. Hypertriglyceridemia can cause acute pancreatitis. Monitor lipids, including TG. Instruct patients to discontinue colesevelam hydrochloride and seek prompt medical attention if the symptoms of acute pancreatitis occur. (5.1)
- Gastrointestinal Obstruction: Cases of bowel obstruction have occurred. Colesevelam hydrochloride is not recommended in patients with gastroparesis, other gastrointestinal motility disorders, and in those who have had major gastrointestinal tract surgery and who may be at risk for bowel obstruction. (5.2)
- Vitamin K or Fat-Soluble Vitamin Deficiencies: Colesevelam hydrochloride may decrease absorption of fat-soluble vitamins. Patients with a susceptibility to deficiencies of vitamin K (e.g., patients on warfarin, patients with malabsorption syndromes) or other fat-soluble vitamins may be at increased risk. Patients on oral vitamin supplementation should take their vitamins at least 4 hours prior to colesevelam hydrochloride. (5.3)
- Drug Interactions: Due to the potential for decreased absorption of other drugs that have not been tested for interaction, consider administering at least 4 hours prior to colesevelam hydrochloride. (5.4, 7, 12.3)

6 ADVERSE REACTIONS

In clinical trials, the most common (incidence ≥ 2% and greater than placebo) adverse reactions with colesevelam hydrochloride included constipation, dyspepsia and nausea. (6.1)

To report SUSPECTED ADVERSE REACTIONS, contact Amneal Pharmaceuticals at 1-877-835-5472 or FDA at 1-800-FDA-1088 or www.fda.gov/medwatch.

7 DRUG INTERACTIONS

Concomitant use with colesevelam hydrochloride may decrease the exposure of the following drugs: Drugs with a narrow therapeutic index (e.g., cyclosporine), phenytoin, thyroid hormone replacement therapy, warfarin, oral contraceptives containing ethinyl estradiol and norethindrone, olmesartan medoxomil, and sulfonylureas (glimepiride, glipizide, glyburide). Administer these drugs 4 hours prior to colesevelam hydrochloride. For patients on warfarin, monitor International Normalized Ratio (INR) frequently during initiation then periodically. (7.1)

Concomitant use with colesevelam hydrochloride may increase the exposure of the following drugs: Metformin extended release. Monitor patient's glycemic control. (7.2)

FULL PRESCRIBING INFORMATION

1 INDICATIONS AND USAGE

1.1 Primary Hyperlipidemia

Colesevelam hydrochloride tablets are indicated as an adjunct to diet and exercise to reduce elevated low-density lipoprotein cholesterol (LDL-C) in adults with primary hyperlipidemia.

Colesevelam hydrochloride tablets are indicated to reduce LDL-C levels in boys and postmenarchal girls, 10 to 17 years of age, with heterozygous familial hypercholesterolemia (HeFH) who are unable to reach LDL-C target levels despite an adequate trial of dietary therapy and lifestyle modification.

1.3 Limitations of Use

- Colesevelam hydrochloride tablets should not be used for the treatment of type 1 diabetes or for the treatment of diabetic ketoacidosis.
- Colesevelam hydrochloride tablets have not been studied in Fredrickson Type I, III, IV, and V dyslipidemias.

2 DOSAGE AND ADMINISTRATION

2.1 Testing Prior to Initiation of Colesevelam Hydrochloride Tablets

Obtain lipid parameters, including triglyceride (TG) levels, before starting colesevelam hydrochloride tablets. Colesevelam hydrochloride tablets are contraindicated in patients with TG levels > 500 mg/dL [see Contraindications (4) and Warnings and Precautions (5.1)].

2.2 Recommended Dosage in Primary Hyperlipidemia

The recommended dosage of colesevelam hydrochloride tablets for adults and for boys and postmenarchal girls aged 10 to 17 years with primary hyperlipidemia is 3.75 grams daily. Colesevelam hydrochloride tablets should be taken as follows:

Tablets
Take 6 tablets once daily or 3 tablets twice daily. Due to tablet size, colesevelam hydrochloride for oral suspension is recommended for use in the pediatric population.

2.3 Important Dosing Information for Primary Hyperlipidemia

Colesevelam hydrochloride can be dosed at the same time as a statin, or colesevelam hydrochloride and the statin can be dosed apart. Monitor lipid levels within 4 to 6 weeks after initiation of colesevelam hydrochloride.

2.4 Administration Instructions

Tablets:
Take colesevelam hydrochloride tablets with a meal and liquid. For patients with difficulty swallowing tablets, use colesevelam hydrochloride for oral suspension [see Warnings and Precautions (5.2)].

3 DOSAGE FORMS AND STRENGTHS

- 625 mg tablets are off-white to pale yellow film-coated oval tablets, debossed with “L61” on one side and plain on the other side.

4 CONTRAINDICATIONS

Colesevelam hydrochloride is contraindicated in patients with:

- Serum TG concentrations > 500 mg/dL [see Warnings and Precautions (5.1)]
- History of hypertriglyceridemia-induced pancreatitis [see Warnings and Precautions (5.1)]
- A history of bowel obstruction [see Warnings and Precautions (5.2)]

5 WARNINGS AND PRECAUTIONS

5.1 Hypertriglyceridemia and Pancreatitis

Colesevelam hydrochloride, like other bile acid sequestrants, can increase serum TG concentrations. Hypertriglyceridemia can cause acute pancreatitis.

Colesevelam hydrochloride had effects on serum TG (median increase 5% compared to placebo) in trials of patients with primary hyperlipidemia.

Obtain lipid parameters, including TG levels, before starting colesevelam hydrochloride and periodically thereafter. Colesevelam hydrochloride is contraindicated in patients with TG levels > 500 mg/dL or patients with a history of hypertriglyceridemia-induced pancreatitis [see Contraindications (4)]. Patients with TG levels greater than 300 mg/dL could have greater increases in serum TG levels with colesevelam hydrochloride and may require additional TG monitoring. Instruct patients to discontinue colesevelam hydrochloride and seek prompt medical attention if the symptoms of acute pancreatitis occur (e.g., severe abdominal pain with or without nausea and vomiting). Discontinue colesevelam hydrochloride if TG levels exceed 500 mg/dL [see Adverse Reactions (6.1)].

5.2 Gastrointestinal Obstruction

Post-marketing cases of bowel obstruction have occurred with colesevelam hydrochloride [see Adverse Reactions (6.2)]. Because of its constipating effects, colesevelam hydrochloride is not recommended in patients with gastroparesis, other gastrointestinal motility disorders, and in those who have had major gastrointestinal tract surgery and who may be at risk for bowel obstruction. Colesevelam hydrochloride is contraindicated in patients with a history of bowel obstruction [see Contraindications (4)]. Instruct patients to promptly discontinue colesevelam hydrochloride and seek medical attention if severe abdominal pain or severe constipation occurs.

Because of the tablet size, colesevelam hydrochloride tablets can cause dysphagia or esophageal obstruction. For patients with difficulty swallowing tablets use colesevelam hydrochloride for oral suspension.

5.3 Vitamin K or Fat-Soluble Vitamin Deficiencies

Colesevelam hydrochloride may decrease the absorption of fat-soluble vitamins A, D, E, and K. Patients with a susceptibility to deficiencies of vitamin K (e.g., patients on warfarin, patients with malabsorption syndromes) or other fat-soluble vitamins may be at increased risk when taking colesevelam hydrochloride.

Patients on oral vitamin supplementation should take their vitamins at least 4 hours prior to colesevelam hydrochloride [see Drug Interactions (7.1)].

5.4 Drug Interactions

Colesevelam hydrochloride reduces gastrointestinal absorption of some drugs. Administer drugs with a known interaction at least 4 hours prior to colesevelam hydrochloride [see Drug Interactions (7)].

Due to the potential for decreased absorption of other drugs that have not been tested for interaction, especially those with a narrow therapeutic index, consider administering at least 4 hours prior to colesevelam hydrochloride [see Clinical Pharmacology (12.3)].

6 ADVERSE REACTIONS

The following important adverse reactions are described below and elsewhere in the labeling:

- Hypertriglyceridemia and Pancreatitis [see Warnings and Precautions (5.1)]
- Gastrointestinal Obstruction [see Warnings and Precautions (5.2)]
- Vitamin K or Fat-Soluble Vitamin Deficiencies [see Warnings and Precautions (5.3)]

6.1 Clinical Studies Experience

Because clinical studies are conducted under widely varying conditions, adverse reaction rates observed in the clinical studies of a drug cannot be directly compared to rates in clinical studies of another drug and may not reflect the rates observed in practice.

Primary Hyperlipidemia
In 7 double-blind, placebo-controlled, clinical trials, 807 patients with primary hyperlipidemia (age range 18 to 86 years, 50% women, 90% Caucasians, 7% Blacks, 2% Hispanics, 1% Asians) and elevated LDL-C were treated with colesevelam hydrochloride 1.5 g/day to 4.5 g/day from 4 to 24 weeks (total exposure 199 patient-years).

Table 1: Clinical Studies of Colesevelam Hydrochloride for Primary Hyperlipidemia: Adverse Reactions Reported in ≥ 2% of Patients and More Commonly than in Placebo
 | Colesevelam Hydrochloride | Placebo
 | N = 807 | N = 258
Constipation | 11.0% | 7.0%
Dyspepsia | 8.3% | 3.5%
Nausea | 4.2% | 3.9%
Accidental injury | 3.7% | 2.7%
Asthenia | 3.6% | 1.9%
Pharyngitis | 3.2% | 1.9%
Flu syndrome | 3.2% | 3.1%
Rhinitis | 3.2% | 3.1%
Myalgia | 2.1% | 0.4%

Pediatric Patients 10 to 17 Years of Age
In an 8-week double-blind, placebo-controlled study boys and post-menarchal girls, 10 to 17 years of age, with HeFH (n=194), were treated with colesevelam hydrochloride tablets (1.9 to 3.8 g, daily) or placebo tablets.

Table 2: Clinical Study of Colesevelam Hydrochloride for Primary Hyperlipidemia in HeFH Pediatric Patients: Adverse Reactions Reported in ≥ 2% of Patients and More Commonly than in Placebo
 | Colesevelam Hydrochloride | Placebo
 | N = 129 | N = 65
Nasopharyngitis | 6.2% | 4.6%
Headache | 3.9% | 3.1%
Fatigue | 3.9% | 1.5%
Creatine Phosphokinase Increase | 2.3% | 0.0%
Rhinitis | 2.3% | 0.0%
Vomiting | 2.3% | 1.5%

The reported adverse reactions during the additional 18-week open-label treatment period with colesevelam hydrochloride 3.8 g per day were similar to those during the double-blind period and included headache (7.6%), nasopharyngitis (5.4%), upper respiratory tract infection (4.9%), influenza (3.8%), and nausea (3.8%).

6.2 Post-marketing Experience

The following additional adverse reactions have been identified during post-approval use of colesevelam hydrochloride. Because these reactions are reported voluntarily from a population of uncertain size, it is generally not possible to reliably estimate their frequency or establish a causal relationship to drug exposure.

Adverse Reactions Resulting from Drug Interactions [see Drug Interactions (7)]:
Increased seizure activity or decreased phenytoin levels in patients receiving phenytoin, reduced International Normalized Ratio (INR) in patients receiving warfarin therapy, and elevated thyroid-stimulating hormone (TSH) in patients receiving thyroid hormone replacement therapy.

Gastrointestinal: Bowel obstruction (in patients with a history of bowel obstruction or resection), dysphagia or esophageal obstruction (occasionally requiring medical intervention), fecal impaction, pancreatitis, abdominal distension, exacerbation of hemorrhoids, and increased transaminases.

Laboratory Abnormalities:Hypertriglyceridemia

7 DRUG INTERACTIONS

7.1 Colesevelam Hydrochloride Drug Interactions that Decrease the Exposure of the Concomitant Medication

Table 4 includes a list of drugs that decrease exposure of the concomitant medication when administered concomitantly with colesevelam hydrochloride and instructions for preventing or managing them.

Table 4: Colesevelam Hydrochloride Drug Interactions that Decrease the Exposure of the Concomitant Medication
Drugs with a Narrow Therapeutic Index
Clinical Impact: | Concomitant use with colesevelam hydrochloride may decrease the exposure of the narrow therapeutic index drug. In vivo drug interactions studies showed a decrease in exposure of cyclosporine when co-administered with colesevelam hydrochloride [see Clinical Pharmacology (12.3)].
Intervention: | Administer the narrow therapeutic index drug at least 4 hours prior to colesevelam hydrochloride. Monitor drug levels when appropriate.
Examples: | Cyclosporine
Phenytoin
Clinical Impact: | There have been post-marketing reports of increased seizure activity or decreased phenytoin levels in patients receiving phenytoin [see Adverse Reactions (6.2)].
Intervention: | Administer phenytoin 4 hours prior to colesevelam hydrochloride.
Thyroid Hormone Replacement Therapy
Clinical Impact: | In vivo drug interactions studies showed a decrease in exposure of levothyroxine when co-administered with colesevelam hydrochloride [see Clinical Pharmacology (12.3)]. There have been post-marketing reports of elevated thyroid-stimulating hormone (TSH) in patients receiving thyroid hormone replacement therapy [see Adverse Reactions (6.2)].
Intervention: | Administer thyroid hormone replacement therapy 4 hours prior to colesevelam hydrochloride.
Warfarin
Clinical Impact: | There have been post-marketing reports of reduced INR in patients receiving warfarin therapy [see Adverse Reactions (6.2)].
Intervention: | Monitor INR frequently during colesevelam hydrochloride initiation then periodically thereafter.
Oral Contraceptives Containing Ethinyl Estradiol and Norethindrone
Clinical Impact: | In vivo drug interactions studies showed a decrease in exposure of ethinyl estradiol and norethindrone when co-administered with colesevelam hydrochloride [see Clinical Pharmacology (12.3)].
Intervention: | Administer oral contraceptives containing ethinyl estradiol and norethindrone 4 hours prior to colesevelam hydrochloride.
Olmesartan Medoxomil
Clinical Impact: | In vivo drug interactions studies showed a decrease in olmesartan medoxomil when co-administered with colesevelam hydrochloride [see Clinical Pharmacology (12.3)].
Intervention: | Administer olmesartan medoxomil 4 hours prior to colesevelam hydrochloride.
Sulfonylureas
Clinical Impact: | In vivo drug interactions studies showed a decrease in sulfonylureas when co-administered with colesevelam hydrochloride [see Clinical Pharmacology (12.3)].
Intervention: | Administer sulfonylureas 4 hours prior to colesevelam hydrochloride.
Examples: | Glimepiride, glipizide, and glyburide
Oral Vitamin Supplements
Clinical Impact: | Colesevelam hydrochloride may decrease the absorption of fat-soluble vitamins A, D, E, and K [see Warnings and Precautions (5.3)].
Intervention: | Patients on oral vitamin supplementation should take their vitamins at least 4 hours prior to colesevelam hydrochloride.

7.2 Colesevelam Hydrochloride Drug Interactions that Increase the Exposure of the Concomitant Medication

Table 5: Colesevelam Hydrochloride Drug Interactions that Increase the Exposure of the Concomitant Medication
Metformin Extended-Release (ER)
Clinical Impact: | In vivo drug interactions studies showed an increase in metformin extended release (ER) when co-administered with colesevelam hydrochloride [see Clinical Pharmacology (12.3)].
Intervention: | Monitor patients’ glycemic control.

8 USE IN SPECIFIC POPULATIONS

8.1 Pregnancy

Risk Summary
Colesevelam hydrochloride is not absorbed systemically following oral administration, and maternal use is not expected to result in fetal exposure to the drug. Limited available data on the use of colesevelam hydrochloride are insufficient to determine a drug-associated risk of major congenital malformations or miscarriage. In animal reproduction studies, no evidence of either maternal or fetal toxicity was found in rats or rabbits exposed to colesevelam hydrochloride during the period of fetal organogenesis at 8 and 5 times, respectively, the maximum recommended human dose (MRHD) of 3.75 g/day, based on body surface area (mg/m^2). No adverse effects on offspring survival and development were observed in rats administered 5 times the MRHD (see Data). Colesevelam hydrochloride may decrease the absorption of fat-soluble vitamins [see Warnings and Precautions (5.3)]. There are no data available on the effect of colesevelam hydrochloride on the absorption of fat-soluble vitamins in pregnant women. If the patient becomes pregnant while taking colesevelam hydrochloride, the patient should be advised of the lack of known clinical benefit with continued use during pregnancy.

The estimated background risk of major birth defects and miscarriage for the indicated population is unknown. In the US general population, the estimated background risk of major birth defects and miscarriage in clinically recognized pregnancies is 2% to 4% and 15% to 20%, respectively.

Data
Human Data
There are no adequate and well-controlled studies of colesevelam hydrochloride use in pregnant women. In the post-marketing setting there have been infrequent reports of pregnancy with use of colesevelam hydrochloride and a causal association with congenital anomalies has not been established.

Animal Data
In pregnant rats given dietary doses of 0.3, 1.0, 3.0 g/kg/day colesevelam hydrochloride from gestation days 7 through 17, no teratogenic effects were observed. Exposures at 3.0 g/kg/day were 8 times the human exposure at 3.75 g/day MRHD, based on body surface area (mg/m^2).

In pregnant rabbits given oral gavage doses of 0.1, 0.5, 1.0 g/kg/day colesevelam hydrochloride from gestation days 6 through 18, no teratogenic effects were observed. Exposures at 1.0 g/kg/day were 5 times the human exposure at 3.75 g/day MRHD, based on body surface area (mg/m^2).

In pregnant rats given oral gavage doses of 0.1, 0.3, 1.0 g/kg/day colesevelam hydrochloride from gestation day 6 through lactation day 21 (weaning), no adverse effects on survival and development were observed. Exposures at 1.0 g/kg/day were 5 times the human exposure at 3.75 g/day MRHD, based on body surface area (mg/m^2).

8.2 Lactation

Risk Summary
Colesevelam hydrochloride is not absorbed systemically by the mother following oral administration, and breastfeeding is not expected to result in exposure of the child to colesevelam hydrochloride.

8.3 Females and Males of Reproductive Potential

Contraception
Use of colesevelam hydrochloride may reduce the efficacy of oral contraceptives. Advise patients to take oral contraceptives at least 4 hours prior to taking colesevelam hydrochloride [see Drug Interactions (7)].

8.4 Pediatric Use

Primary Hyperlipidemia
The safety and effectiveness of colesevelam hydrochloride to reduce LDL-C levels in boys and postmenarchal girls 10 to 17 years of age with HeFH who are unable to reach LDL-C target levels despite an adequate trial of dietary therapy and lifestyle modification have been established. Use of colesevelam hydrochloride for this indication is supported by a study in 129 colesevelam hydrochloride -treated pediatric patients aged 10 to 17 years with HeFH [see Clinical Studies (14.1)]. Adverse reactions commonly observed in pediatric patients compared to placebo, but not in adults, included headache (3.9%), creatine phosphokinase increase (2.3%), and vomiting (2.3%) [see Adverse Reactions (6.1)]. There were no significant effects on fat-soluble vitamin levels or clotting factors in the adolescent boys or girls relative to placebo. Due to colesevelam hydrochloride tablet size, colesevelam hydrochloride for oral suspension is recommended for use in the pediatric population [see Dosage and Administration (2.2, 2.4)]. The safety and effectiveness of colesevelam hydrochloride in pediatric patients with HeFH less than 10 years of age or in premenarchal females have not been established.

8.5 Geriatric Use

Primary Hyperlipidemia
Of the 1,350 patients enrolled in the hyperlipidemia clinical studies, 349 (26%) were ≥65 years old, and 58 (4%) were ≥75 years old. No overall differences in safety or effectiveness were observed between these subjects and younger subjects, and other reported clinical experience has not identified differences in responses between the elderly and younger patients, but greater sensitivity of some older individuals cannot be ruled out.

10 OVERDOSAGE

Colesevelam hydrochloride is not absorbed and the risk of systemic toxicity is low. Excessive doses of colesevelam hydrochloride may cause more severe local gastrointestinal effects (e.g., constipation).

11 DESCRIPTION

Colesevelam hydrochloride is a non-absorbed, polymeric, lipid-lowering and glucose-lowering agent for oral administration. Colesevelam hydrochloride is a high-capacity bile acid-binding molecule.

Colesevelam hydrochloride is poly (allylamine hydrochloride) cross-linked with epichlorohydrin and alkylated with 1-bromodecane and (6-bromohexyl)-trimethylammonium bromide. The chemical name (IUPAC) of colesevelam hydrochloride is allylamine polymer with 1-chloro-2,3-epoxypropane, [6-(allylamino)-hexyl]trimethylammonium chloride and N-allyldecylamine, hydrochloride. The chemical structure of colesevelam hydrochloride is represented by the following formula:

wherein (a) represents allyl amine monomer units that have not been alkylated by either of the 1-bromodecane or (6-bromohexyl)-trimethylammonium bromide alkylating agents or cross-linked by epichlorohydrin; (b) represents allyl amine units that have undergone cross-linking with epichlorohydrin; (c) represents allyl amine units that have been alkylated with a decyl group; (d) represents allyl amine units that have been alkylated with a (6-trimethylammonium) hexyl group, and m represents a number ≥ 100 to indicate an extended polymer network. A small amount of the amines are dialkylated and are not depicted in the formula above. No regular order of the groups is implied by the structure; cross-linking and alkylation are expected to occur randomly along the polymer chains. A large amount of the amines are protonated. The polymer is depicted in the hydrochloride form; a small amount of the halides are bromide. Colesevelam hydrochloride is hydrophilic and insoluble in water.

Colesevelam hydrochloride tablets are an off-white to pale yellow film-coated, oval tablets, debossed with “L61” on one side and plain on the other side, containing 625 mg colesevelam hydrochloride. In addition, each tablet contains the following inactive ingredients: colloidal silicon dioxide, copovidone, hypromellose, magnesium stearate, microcrystalline cellulose, polyethylene glycol, and talc.

12 CLINICAL PHARMACOLOGY

12.1 Mechanism of Action

Primary Hyperlipidemia: Colesevelam hydrochloride, the active pharmaceutical ingredient in colesevelam hydrochloride tablets, is a non-absorbed, lipid-lowering polymer that binds bile acids in the intestine, impeding their reabsorption. As the bile acid pool becomes depleted, the hepatic enzyme, cholesterol 7-α-hydroxylase, is upregulated, which increases the conversion of cholesterol to bile acids. This causes an increased demand for cholesterol in the liver cells, resulting in the dual effect of increasing transcription and activity of the cholesterol biosynthetic enzyme, HMG-CoA reductase, and increasing the number of hepatic LDL receptors. These compensatory effects result in increased clearance of LDL-C from the blood, resulting in decreased serum LDL-C levels. Serum TG levels may increase or remain unchanged.

12.2 Pharmacodynamics

A maximum therapeutic response to the lipid-lowering effects of colesevelam hydrochloride was achieved within 2 weeks and was maintained during long-term therapy.

12.3 Pharmacokinetics

Absorption
Colesevelam hydrochloride is a hydrophilic, water-insoluble polymer that is not hydrolyzed by digestive enzymes and is not absorbed.

Distribution
Colesevelam hydrochloride is not absorbed, and therefore, its distribution is limited to the gastrointestinal tract.

Elimination
Metabolism
Colesevelam hydrochloride is not metabolized systemically and does not interfere with systemic drug-metabolizing enzymes such as cytochrome P450.

Excretion
In 16 healthy volunteers, an average of 0.05% of administered radioactivity from a single^14C-labeled colesevelam hydrochloride dose was excreted in the urine.

Drug Interaction Studies
Drug interactions between colesevelam and concomitantly administered drugs were screened through in vitro studies and confirmed in in vivo studies. In vitro studies demonstrated that cephalexin, metformin, and ciprofloxacin had negligible binding to colesevelam hydrochloride. Therefore, an in vivo pharmacokinetic interaction of colesevelam hydrochloride with these drugs is unlikely. Colesevelam hydrochloride was found to have no significant effect on the bioavailability of aspirin, atenolol, digoxin, enalapril, fenofibrate, lovastatin, metoprolol, phenytoin, pioglitazone, quinidine, rosiglitazone, sitagliptin, valproic acid, and warfarin. The results of additional in vivo drug interactions of colesevelam hydrochloride are presented in Table 6.

Table 6: Mean Change in Drug Exposure (AUC0-∞and Cmax) when Administered with Colesevelam Hydrochloride (3.75 g) [With verapamil, the dose of colesevelam hydrochloride was 4.5 g]
Drug | Dose | Co-administered |  | 1 hr prior to Colesevelam Hydrochloride |  | 4 hrs prior to Colesevelam Hydrochloride
Drug | Dose | AUC0-∞ | Cmax | AUC0-∞ | Cmax | AUC0-∞ | Cmax
Cyclosporine | 200 mg | -34% | -44% | N/A | N/A | N/A | N/A
Ethinyl Estradiol [Oral contraceptive containing norethindrone and ethinyl estradiol] | 0.035 mg | -24% | -24% | -18% | -1% | -12% | 0%
Glimepiride | 4 mg | -18% | -8% | N/A | N/A | -6% | 3%
Glipizide | 20 mg | -12% | -13% | N/A | N/A | -4% | 0%
Glyburide | 3 mg | -32% | -47% | -20% | -15% | -7% | 4%
Levothyroxine | 600 mcg | -22% | -33% | 6% | -2% | 1% | 8%
Metformin ER | 1500 mg | 44% | 8% | N/A | N/A | N/A | N/A
Norethindrone | 1 mg | -1% | -20% | 5% | -3% | 6% | 7%
Olmesartan Medoxomil | 40 mg | -39% | -28% | N/A | N/A | -15% | -4%
Repaglinide | 2 mg | -7% | -19% | -6% | -1% | N/A | N/A
Verapamil sustained-release | 240 mg | -31% | -11% | N/A | N/A | N/A | N/A
N/A – Not Available

13 NONCLINICAL TOXICOLOGY

13.1 Carcinogenesis, Mutagenesis, Impairment of Fertility

Carcinogenesis
A 104-week carcinogenicity study with colesevelam hydrochloride was conducted in CD-1 mice, at oral dietary doses up to 3 g/kg/day. This dose was approximately 50 times the maximum recommended human dose of 4.5 g/day, based on body weight, mg/kg. There were no significant drug-induced tumor findings in male or female mice. In a 104-week carcinogenicity study with colesevelam hydrochloride in Harlan Sprague-Dawley rats, a statistically significant increase in the incidence of pancreatic acinar cell adenoma was seen in male rats at doses > 1.2 g/kg/day (approximately 20 times the maximum human dose, based on body weight, mg/kg) (trend test only). A statistically significant increase in thyroid C-cell adenoma was seen in female rats at 2.4 g/kg/day (approximately 40 times the maximum human dose, based on body weight, mg/kg).

Mutagenesis
Colesevelam hydrochloride and 4 degradants present in the drug substance have been evaluated for mutagenicity in the Ames test and a mammalian chromosomal aberration test. The 4 degradants and an extract of the parent compound did not exhibit genetic toxicity in an in vitro bacterial mutagenesis assay in S. typhimurium and E. coli (Ames assay) with or without rat liver metabolic activation. An extract of the parent compound was positive in the Chinese Hamster Ovary (CHO) cell chromosomal aberration assay in the presence of metabolic activation and negative in the absence of metabolic activation. The results of the CHO cell chromosomal aberration assay with 2 of the 4 degradants, decylamine HCl and aminohexyltrimethyl ammonium chloride HCl, were equivocal in the absence of metabolic activation and negative in the presence of metabolic activation. The other 2 degradants, didecylamine HCl and 6-decylamino-hexyltrimethyl ammonium chloride HCl, were negative in the presence and absence of metabolic activation.

Impairment of Fertility
Colesevelam hydrochloride did not impair fertility in rats at doses up to 3 g/kg/day (approximately 50 times the maximum human dose, based on body weight, mg/kg).

13.2 Animal Toxicology and/or Pharmacology

Reproductive Toxicology Studies
Reproduction studies have been performed in rats and rabbits at doses up to 3 g/kg/day and 1 g/kg/day, respectively (approximately 50 and 17 times the maximum human dose, based on body weight, mg/kg) and have revealed no evidence of harm to the fetus due to colesevelam hydrochloride.

14 CLINICAL STUDIES

14.1 Primary Hyperlipidemia

Colesevelam hydrochloride reduces total cholesterol (TC), LDL-C, apolipoprotein B (Apo B), and non-high-density lipoprotein cholesterol (non-HDL-C) when administered alone or in combination with a statin in patients with primary hyperlipidemia.

Approximately 1,600 patients were studied in 9 clinical trials with treatment durations ranging from 4 to 50 weeks. With the exception of one open-label, uncontrolled, long-term extension study, all studies were multicenter, randomized, double-blind, and placebo-controlled. A maximum therapeutic response to colesevelam hydrochloride was achieved within 2 weeks and was maintained during long-term therapy.

Monotherapy
In a study in patients with LDL-C between 130 mg/dL and 220 mg/dL (mean 158 mg/dL), colesevelam hydrochloride was given for 24 weeks in divided doses with the morning and evening meals.

As shown in Table 7, the mean LDL-C reductions were 15% and 18% at the 3.8 g and 4.5 g doses. The respective mean TC reductions were 7% and 10%. The mean Apo B reductions were 12% in both treatment groups. Colesevelam hydrochloride at both doses increased HDL-C by 3%. Increases in TG of 9% to 10% were observed at both colesevelam hydrochloride doses but the changes were not statistically different from placebo.

Table 7: Response to Colesevelam Hydrochloride Monotherapy in a 24-Week Trial – Percent Change in Lipid Parameters from Baseline
Grams/Day | N | TC | LDL-C | Apo B | HDL-C [Median % change from baseline.] | Non-HDL-C | TG
Placebo | 88 | +1 | 0 | 0 | –1 | +1 | +5
3.8 g (6 tablets) | 95 | –7 [p < 0.05 for lipid parameters compared to placebo, for Apo B compared to baseline.] | –15 | –12 | +3 | –10 | +10
4.5 g (7 tablets) | 94 | –10 | –18 | –12 | +3 | –13 | +9

In a study in 98 patients with LDL-C between 145 mg/dL and 250 mg/dL (mean 169 mg/dL), colesevelam hydrochloride 3.8 g was given for 6 weeks as a single-dose with breakfast, as a single-dose with dinner, or as divided doses with breakfast and dinner. The mean LDL-C reductions were 18%, 15%, and 18% for the 3 dosing regimens, respectively. The reductions with these 3 regimens were not statistically different from one another.

Combination Therapy
Co-administration of colesevelam hydrochloride and a statin (atorvastatin, lovastatin, or simvastatin) in 3 clinical studies demonstrated an additive reduction of LDL-C. The mean baseline LDL-C was 184 mg/dL in the atorvastatin study (range 156 mg/dL to 236 mg/dL), 171 mg/dL in the lovastatin study (range 115 mg/dL to 247 mg/dL), and 188 mg/dL in the simvastatin study (range 148 mg/dL to 352 mg/dL). As demonstrated in Table 8, colesevelam hydrochloride doses of 2.3 g to 3.8 g resulted in an additional 8% to 16% reduction in LDL-C above that seen with the statin alone.

Table 8: Response to Colesevelam Hydrochloride in Combination with Atorvastatin, Simvastatin, or Lovastatin - Percent Change in Lipid Parameters
Dose/Day | N | TC | LDL-C | Apo B | HDL-C [Median % change from baseline.] | Non-HDL-C | TG
Atorvastatin Trial (4-week)
Placebo | 19 | +4 | +3 | –3 | +4 | +4 | +10
Atorvastatin 10 mg | 18 | –27 [p < 0.05 for lipid parameters compared to placebo, for Apo B compared to baseline.] | –38 | –32 | +8 | –35 | –24
Colesevelam hydrochloride 3.8 g/ Atorvastatin 10 mg | 18 | –31 | –48 | –38 | +11 | –40 | –1
Atorvastatin 80 mg | 20 | –39 | –53 | –46 | +6 | –50 | –33
Simvastatin Trial (6-week)
Placebo | 33 | –2 | –4 | –4 | –3 | –2 | +6
Simvastatin 10 mg | 35 | –19 | –26 | –20 | +3 | –24 | –17
Colesevelam hydrochloride 3.8 g/ Simvastatin 10 mg | 34 | –28 | –42 | –33 | +10 | –37 | –12
Simvastatin 20 mg | 39 | –23 | –34 | –26 | +7 | –30 | –12
Colesevelam hydrochloride 2.3 g/ Simvastatin 20 mg | 37 | –29 | –42 | –32 | +4 | –37 | –12
Lovastatin Trial (4-week)
Placebo | 26 | +1 | 0 | 0 | +1 | +1 | +1
Lovastatin 10 mg | 26 | –14 | –22 | –16 | +5 | –19 | 0
Colesevelam hydrochloride 2.3 g/ Lovastatin 10 mg Together | 27 | –21 | –34 | –24 | +4 | –27 | –1
Colesevelam hydrochloride 2.3 g/ Lovastatin 10 mg Apart | 23 | –21 | –32 | –24 | +2 | –28 | –2

In all 3 studies, the LDL-C reduction achieved with the combination of colesevelam hydrochloride and any given dose of statin therapy was statistically superior to that achieved with colesevelam hydrochloride or that dose of the statin alone. The LDL-C reduction with atorvastatin 80 mg was not statistically significantly different from the combination of colesevelam hydrochloride 3.8 g and atorvastatin 10 mg.

Pediatric Therapy
The safety and efficacy of colesevelam hydrochloride in pediatric patients were evaluated in an 8-week, multicenter, randomized, double-blind, placebo-controlled, parallel-group study followed by an open-label phase, in 194 boys and postmenarchal girls 10 to 17 years of age (mean age 14.1 years) with HeFH, taking a stable dose of an FDA-approved statin (with LDL-C > 130 mg/dL) or naïve to lipid-lowering therapy (with LDL-C > 160 mg/dL). This study had 3 periods: a single-blind, placebo stabilization period; an 8-week, randomized, double-blind, parallel-group, placebo-controlled treatment period; and an 18-week, open-label treatment period. Forty-seven (24%) patients were taking statins and 147 (76%) patients were statin-naïve at screening. The mean baseline LDL-C at Day 1 was approximately 199 mg/dL.

During the double-blind treatment period, patients were assigned randomly to treatment: Colesevelam hydrochloride 3.8 g/day (n=64), colesevelam hydrochloride 1.9 g/day (n=65), or placebo (n=65). In total, 186 patients completed the double-blind treatment period. After 8 weeks of treatment, colesevelam hydrochloride 3.8 g/day significantly decreased plasma levels of LDL-C, non-HDL-C, TC, and Apo B and significantly increased HDL-C. A moderate, non-statistically significant increase in TG was observed versus placebo (Table 9).

Table 9: Response to Colesevelam Hydrochloride 3.8 g Compared to Placebo in Pediatric Patients 10 to 17 Years of Age – Mean Percent Change in Lipid Parameters from Baseline to Week 8
Treatment Difference | TC | LDL-C | Apo B | HDL-C | Non-HDL-C | TG [For triglycerides, median % change from baseline.]
Treatment Difference | (N=128) | (N=128) | (N=124) | (N=128) | (N=128) | (N=128)
Colesevelam hydrochloride 3.8 g vs. Placebo | -7 [p≤0.05 for lipid parameters compared to placebo] | -13 | -8 | +6 | –11 | +5
Values represent LS mean. Only patients with values at both study baseline and endpoint are included in this table. Study baseline was defined as the last value measured before or on Day 1 prior to the first dose of randomized study medication.
Results were based on the ITT population with LOCF

During the open-label treatment period patients were treated with colesevelam hydrochloride 3.8 g/day. In total, 173 (89%) patients completed 26 weeks of treatment. Results at Week 26 were consistent with those at Week 8.

16 HOW SUPPLIED/STORAGE AND HANDLING

Colesevelam Hydrochloride Tablets, 625 mg are supplied as off-white to pale yellow film-coated oval tablets, debossed with “L61” on one side and plain on the other side. Colesevelam hydrochloride tablets are available as follows:
Unit dose packages of 30 (5 x 6) NDC 60687-385-25

Store at 20° to 25°C (68° to 77°F) [see USP Controlled Room Temperature]. Protect from moisture.

FOR YOUR PROTECTION: Do not use if blister is torn or broken.

17 PATIENT COUNSELING INFORMATION

Hypertriglyceridemia and Pancreatitis:
Inform patients that colesevelam hydrochloride may increase their serum triglycerides which can lead to hypertriglyceridemia and pancreatitis. Instruct patients to discontinue colesevelam hydrochloride and seek prompt medical attention if the symptoms of acute pancreatitis occur (e.g., severe abdominal pain with or without nausea and vomiting) [see Warnings and Precautions (5.1)].

Gastrointestinal
Inform patients that colesevelam hydrochloride may cause bowel obstruction. Instruct patients to promptly discontinue colesevelam hydrochloride and seek medical attention if severe abdominal pain or severe constipation occurs [see Warnings and Precautions (5.2)].

Drug and Vitamin Interactions
Advise patients that colesevelam hydrochloride has drug interactions and colesevelam hydrochloride may decrease the absorption of fat-soluble vitamins A, D, E, and K. Instruct patients to take oral vitamins at least 4 hours prior to colesevelam hydrochloride. Instruct patients to inform their physician about all the drugs and vitamins that they are prescribed or take over the counter [see Warnings and Precautions (5.3)and Drug Interactions (7)].

Hypertriglyceridemia and Cardiovascular Disease
Inform patients that colesevelam hydrochloride may increase serum triglycerides and that the long-term effect of hypertriglyceridemia on the risk of coronary artery disease is uncertain [see Warnings and Precautions (5.1)].

Administration [see Dosage and Administration (2.4)]
Tablets
Advise patients to take colesevelam hydrochloride tablets with a meal and liquid. Inform patients that colesevelam hydrochloride tablets can be taken as 6 tablets once daily or 3 tablets twice daily.

Females of Reproductive Potential
Advise females of reproductive potential that colesevelam hydrochloride may reduce the effectiveness of oral contraceptives, and to take oral contraceptives at least 4 hours before taking colesevelam hydrochloride [see Drug Interactions (7)and Use in Specific Populations (8.3)].

PACKAGING INFORMATION

American Health Packaging unit dose blisters (see How Supplied section) contain drug product from Amneal Pharmaceuticals LLC as follows:
(625 mg / 30 UD) NDC 60687-385-25 packaged from NDC 0115-1320

Distributed by:
American Health Packaging
Columbus, OH 43217

8438525/1023F

Package/Label Display Panel – Carton – 625 mg

NDC 60687- 385-25

Colesevelam
HydrochlorideTablets

625 mg

30 Tablets (5 x 6) Rx Only

Each Tablet Contains: Active Ingredient:
Colesevelam hydrochloride ......................................625 mg

Usual Dosage: See full prescribing information.

Store at 20° to 25°C (68° to 77°F); excursions permitted
between 15° to 30°C (59° to 86°F) [see USP Controlled
Room Temperature]. Protect from moisture.

FOR YOUR PROTECTION: Do not use if blister is torn
or broken.

The drug product contained in this package is from
NDC # 0115-1320, Amneal Pharmaceuticals LLC.

Distributed by: American Health Packaging, Columbus,
Ohio 43217

738525
0438525/1023

Package/Label Display Panel – Blister – 625 mg

Colesevelam
Hydrochloride
Tablet

625 mg